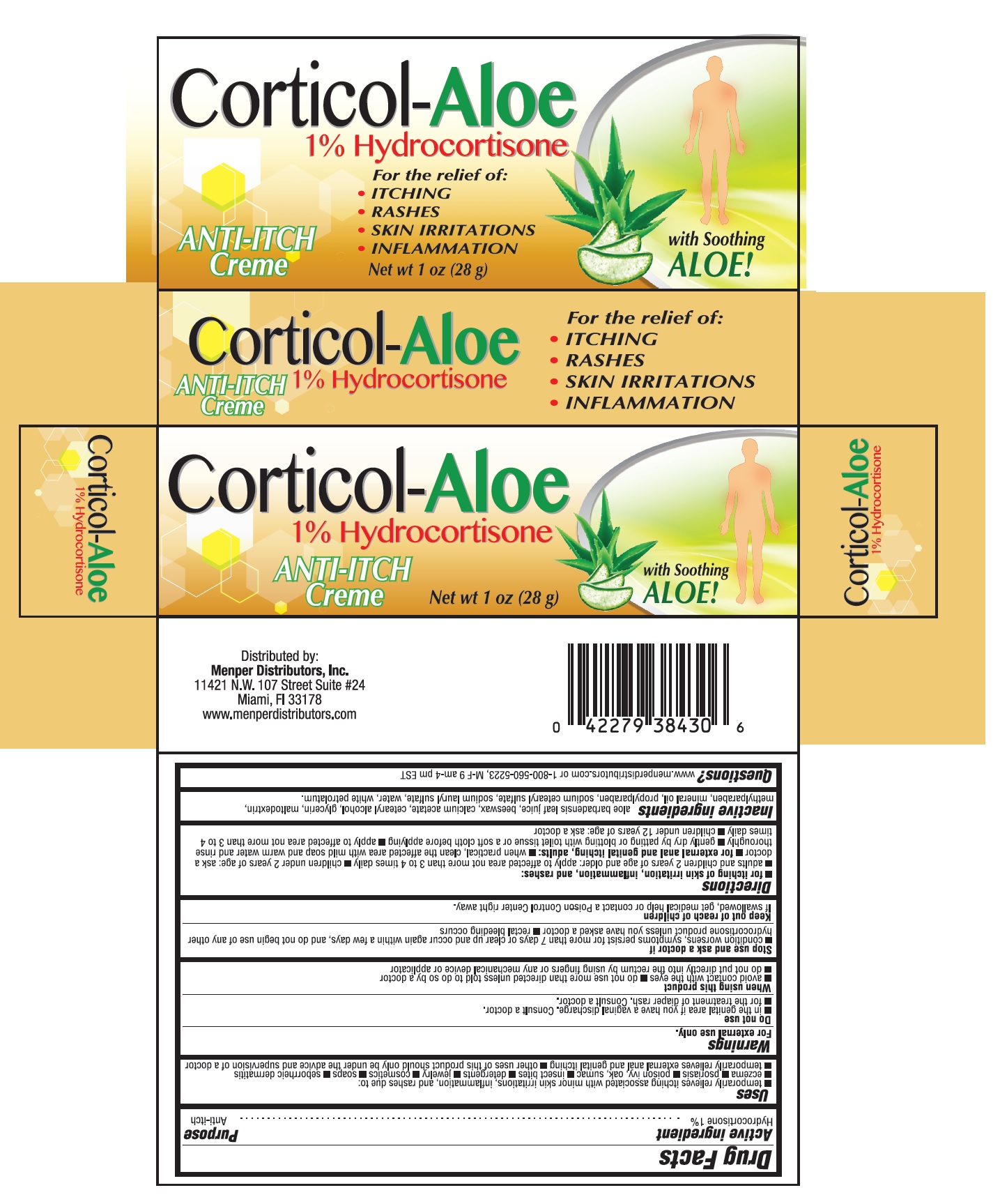 DRUG LABEL: Corticol-Aloe
NDC: 53145-430 | Form: CREAM
Manufacturer: MENPER DISTRIBUTORS INC.
Category: otc | Type: HUMAN OTC DRUG LABEL
Date: 20210809

ACTIVE INGREDIENTS: HYDROCORTISONE 1 g/100 g
INACTIVE INGREDIENTS: ALOE VERA LEAF; SYNTHETIC BEESWAX; CALCIUM ACETATE; CETOSTEARYL ALCOHOL; GLYCERIN; MALTODEXTRIN; METHYLPARABEN; MINERAL OIL; PROPYLPARABEN; SODIUM CETOSTEARYL SULFATE; SODIUM LAURYL SULFATE; WATER; WHITE PETROLATUM

Active Ingredient

Hydrocortisone 1%

Purpose

Anti-itch

Uses

- temproarily relieves itching associated with minor skin irritations, inflammation and rashes due to:
- eczema
- psoriasis
- poison ivy, oak, sumac
- insect bites
- detergents
- jewlery
- cosmetics
- soaps
- seborrheic dermatitis
- temporarily relieves extranal anal and genital itching
- other uses of this product should only be under the advice and supervision of a doctor

Warnings

For external use only.

Do not use

- in the genital area if you have a vaginal discharg. Consult a doctor.
- for the treatment of diaper rash. Consult a doctor

When using this product

- avoid contact with the eyes
- do not use more than directed unless told to do so by a doctor
- do not put directly into the rectum by using fingers or any mechanical device or applicator

Stop use and ask a doctor if

- condition worsen, symptoms persist for more than 7 days or clear up and occur again within a few days, and do not begin use of any other hydrocortisone product unless you have asked a doctor
- rectal bleeding occurs

Keep out of reach of children

If swallowed, get medical help or contact a Poison Control Center right away.

Directions

- for itchin of skin irritiation, inflammation and rashes:
- adults and children 2 years of agea and older: apply to affected area not more than 3 to 4 times daily
- children under 2 years of age: ask a doctor
- for external anal and genital itching, adults
- when practical, clean the affected area with mild soap and warm water and rinse thouroghly
- gently dry by patting or blotting with toilet tissue or a soft cloth before applying
- apply to affected area not more than 3 to 4 times daily
- children under 12 years of age: ask a doctor

Inactive ingredients

aloe barbadensis leaf juice, beeswax, clacium acetate, cetearyl alcohol, glycerin, maltodextrin, mehtylparaben, mineral oil, propylparaben, sodium cetearyl sulfate, sodium lauryl sulfate, water, white petrolatum

Questions

www.menperdistributors.com or 1-800-560-5223 M-F 9 am - 4 pm EST